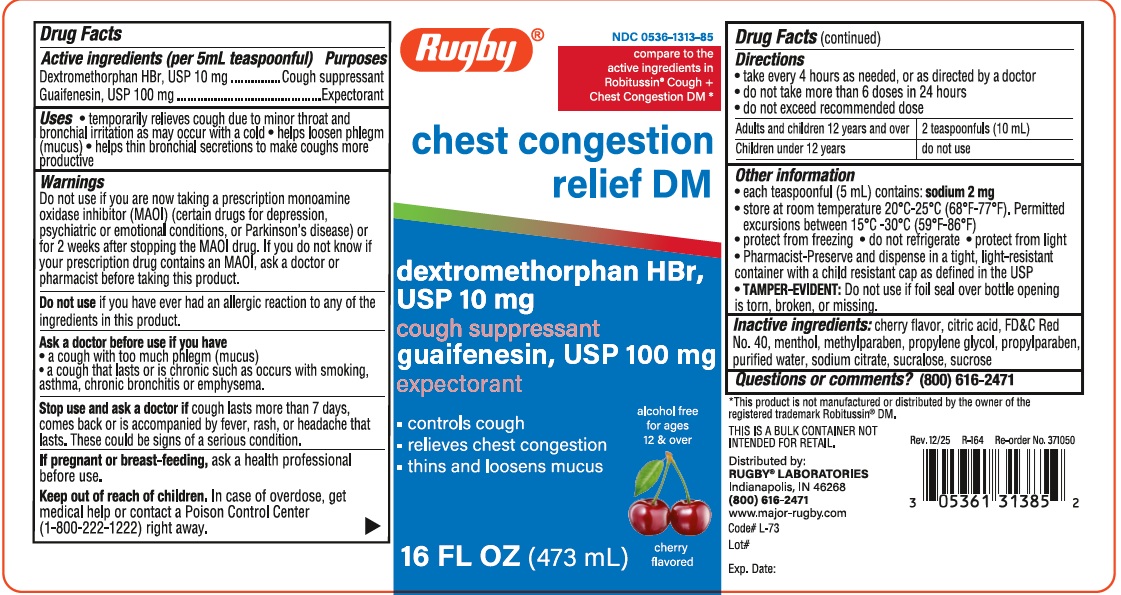 DRUG LABEL: Chest Congestion Relief
NDC: 0536-1313 | Form: LIQUID
Manufacturer: RUGBY LABORATORIES
Category: otc | Type: HUMAN OTC DRUG LABEL
Date: 20251230

ACTIVE INGREDIENTS: DEXTROMETHORPHAN HYDROBROMIDE 10 mg/5 mL; GUAIFENESIN 100 mg/5 mL
INACTIVE INGREDIENTS: CITRIC ACID MONOHYDRATE; FD&C RED NO. 40; MENTHOL; METHYLPARABEN; PROPYLENE GLYCOL; PROPYLPARABEN; WATER; SODIUM CITRATE; SUCRALOSE; SUCROSE

Rugby- Chest Cong DM 1313

Active ingredient

Dextromethorphan HBr, 10 mg

Guaifenesin 100 mg

Purpose

Cough suppressant

Expectorant

Uses

- temporarily relieves cough due to minor thoat and bronchial irritation
- helps loosen phlegm (mucus)
- helps thin bronchial secretions to make coughs more productive

Warnings

Do not use if you are now taking a prescription monoamine oxidase inhibitor (MAOI) (certain drugs for depression, psychiatric or emotional conditions, or Parkinson's disease, psychiatric or emotional conditions, or Parkinson's disease) or for 2 weeks after stopping the MAOI drug. If you do not know if your prescription drug contains an MAOI, ask a doctor or pharmacist before taking this product.

Do not use ifyou have ever had an allergic reaction to any of the ingredients in this product.

Ask a doctor before use if you have

- a cough with too much phlegm (mucus)
- a cough that lasts or is chronic such as occurs with smoking asthma, chronic bronchitis or emphysema.

Stop use and ask a doctor if cough lasts more than 7 days, comes back or is accompanied by fever, rash, or headache that lasts. These could be signs of a serious condition.

PREGNANCY OR BREAST FEEDING

If pregnant or breast feeding, ask a health professional before use.

Keep out of reach of children. In case of overdose, get medical help or contact a Poison Control Center (1-800-222-1222) right away

Directions

- take every 4 hours as needed, or as directed by a doctor
- do not take moer than 6 doses in 24 hours
- do not exceed recommended dose

Adults and children 12 years and over | 2 teasponsfuls (10 mL)
Children under 12 years | do not use

INACTIVE INGREDIENT

Inactive ingredients: Cherry flavor, citric acid, FD&C Red #40, menthol, methylparaben, propylene glycol, propylparaben, water, sodium citrate, sucralose, sucrose.

QUESTIONS

1-800-645-2158

PACKAGE LABEL

13